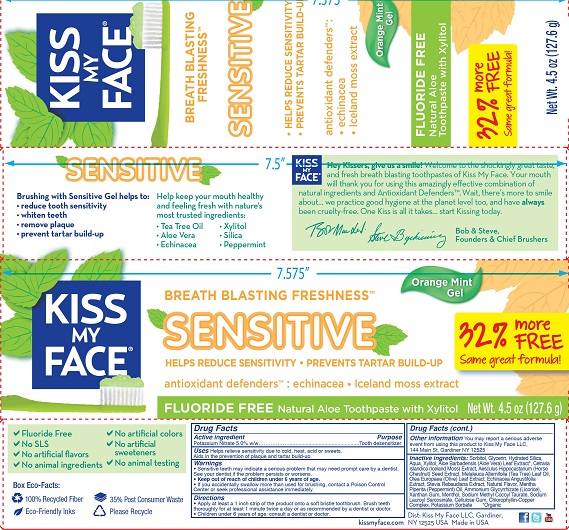 DRUG LABEL: Kiss My Face
NDC: 65364-401 | Form: GEL, DENTIFRICE
Manufacturer: Kiss My Face, LLC
Category: otc | Type: HUMAN OTC DRUG LABEL
Date: 20190220

ACTIVE INGREDIENTS: POTASSIUM NITRATE 5 g/100 g
INACTIVE INGREDIENTS: WATER; CETRARIA ISLANDICA SUBSP. ISLANDICA; SODIUM LAURYL SARCOSINATE; SORBITOL; AESCULUS HIPPOCASTANUM SEED OIL; TEA TREE OIL; GLYCERIN; XANTHAN GUM; HYDRATED SILICA; OLEA EUROPAEA LEAF; SODIUM METHYL COCOYL TAURATE; ALOE VERA LEAF; ECHINACEA ANGUSTIFOLIA LEAF; MENTHOL; POTASSIUM SORBATE; XYLITOL; SODIUM COPPER CHLOROPHYLLIN; STEVIA REBAUDIUNA LEAF; MENTHA PIPERITA; AMMONIUM GLYCYRRHIZATE; CARBOXYMETHYLCELLULOSE SODIUM, UNSPECIFIED FORM

Kiss My Face Sensitive Fluoride Free

Drug Facts

Active ingredient

Potassium Nitrate 5.0% w/w

Purpose

Tooth desensitizer

Uses

Helps relieve sensitivity of the teeth to cold, heat, acids or sweet.

Aids in the prevention of plaque and tarter build-up.

Warnings

- Sensitive teeth may indicate a serious problem that may need prompt care by a dentist. See your dentist if the problem persists or worsens.

- Keep out of reach of children under 6 years of age
- If you accidentally swallow more than used for brushing, contact a Poison Control Center or seek professional assistance immediately.

Directions

- Apply at least a 1 inch strip of the product onto a soft bristle toothbrush. Brush teeth thoroughly for at least one minute, preferably after each meal or at least twice a day or as recommended by a dentist or doctor.
- Children under 6 years of age: consult a dentist or doctor.

Other information

You may report a serious adverse event from using this product to Kiss My Face LLC, 144 Main St, Gardiner NY 12525.

INACTIVE INGREDIENT

Inactive ingredients Sorbitol, Glycerin, Hydrated Silica, Aqua, Xylitol, Aloe Barbadensis (Aloe Vera) Leaf Extract*, Cetraria Islandica (Iceland Moss) Extract, Aesculus Hippocastanum (Horse Chestnut) Seed Extract, Melaleuca Alternifolia (Tea Tree) Leaf Oil, Olea Europaea (Olive) Leaf Extract, Echinacea Angustifolia Extract, Stevia Rebaudiana Extract, Natural Flavor, Mentha Piperita (Peppermint) Oil, Ammonium Glycyrrhizate (Licorice), Xanthan Gum, Menthol, Sodium Methyl Cocoyl Taurate, Sodium Lauroyl Saracosinate, Cellulose Gum, Chlorophyllin-Copper Complex, Potassium Sorbate

*Organic

Dist: Kiss My Face LLC

Gardiner, NY 12525 USA

Made in USA

PACKAGE LABEL

KISS MY FACE

BREATH BLASTING FRESHNESS

SENSITIVE

FLUORIDE FREE Natural Aloe Toothpaste with Xylitol

Orange Mint Gel

HELPS REDUCE SENSITIVITY • PREVENTS TARTAR BUILD-UP

antioxidant defenders™: echinacea • Iceland moss extract

NET WT 4.5 OZ (127.6 g)